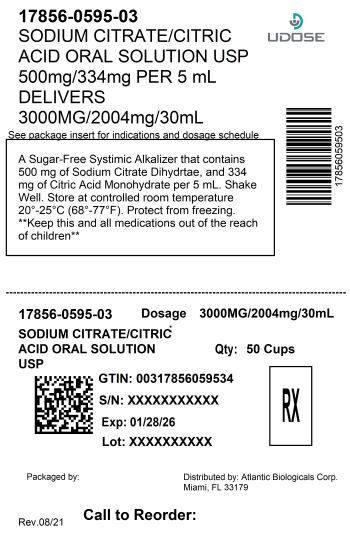 DRUG LABEL: Sodium Citrate and Citric Acid
NDC: 17856-0595 | Form: SOLUTION
Manufacturer: Atlantic Biologicals Corp.
Category: prescription | Type: HUMAN PRESCRIPTION DRUG LABEL
Date: 20260128

ACTIVE INGREDIENTS: SODIUM CITRATE 500 mg/5 mL; ANHYDROUS CITRIC ACID 334 mg/5 mL
INACTIVE INGREDIENTS: POLYETHYLENE GLYCOL, UNSPECIFIED; PROPYLENE GLYCOL; WATER; SODIUM BENZOATE; SORBITOL

Sodium Citrate and Citric Acid Oral Solution USP

A Sugar-Free Systemic Alkalizer

DESCRIPTION

Sodium Citrate and Citric Acid Oral Solution USP is a stable and pleasant-tasting systemic alkalizer containing sodium citrate and citric acid in a sugar-free base. It is a nonparticulate neutralizing buffer.

Sodium Citrate and Citric Acid Oral Solution USP contains in each teaspoonful (5 mL):

SODIUM CITRATE Dihydrate 500 mg (0.34 Molar)
CITRIC ACID Monohydrate 334 mg (0.32 Molar)

Each mL contains 1 mEq sodium ion and is equivalent to 1 mEq bicarbonate (HCO3).

INACTIVE INGREDIENTS: Flavoring, polyethylene glycol, propylene glycol, purified water, sodium benzoate, and sorbitol solution.

CLINICAL PHARMACOLOGY

Sodium citrate is absorbed and metabolized to sodium bicarbonate, thus acting as a systemic alkalizer. The effects are essentially those of chlorides before absorption and those of bicarbonates subsequently. Oxidation is virtually complete so that less than 5% of sodium citrate is excreted in the urine unchanged.

INDICATIONS AND USAGE

Sodium Citrate and Citric Acid Oral Solution USP is an effective alkalinizing agent. It is useful in those conditions where long-term maintenance of an alkaline urine is desirable, and is of value in the alleviation of chronic metabolic acidosis, such as results from chronic renal insufficiency or the syndrome of renal tubular acidosis, especially when the administration of potassium salts is undesirable or contraindicated. This product is also useful for buffering and neutralizing gastric hydrochloric acid quickly and effectively.

Sodium Citrate and Citric Acid Oral Solution USP is concentrated, and when administered after meals and before bedtime, allows one to maintain an alkaline urinary pH around the clock, usually without the necessity of a 2 A.M. dose. This product alkalinizes the urine without producing a systemic alkalosis in the recommended dosage. This product is highly palatable, pleasant tasting, and tolerable, even when administered for long periods.

CONTRAINDICATIONS

Patients on sodium-restricted diets or with severe renal impairment.

PRECAUTIONS

Sodium Citrate and Citric Acid Oral Solution USP should be used with caution by patients with low urinary output unless under the supervision of a physician. This product should not be administered concurrently with aluminum-based antacids. Patients should be directed to dilute adequately with water and preferably, to take each dose after meals to avoid saline laxative effect. Sodium salts should be used cautiously in patients with cardiac failure, hypertension, impaired renal function, peripheral and pulmonary edema, and toxemia of pregnancy. Periodic examinations and determinations of serum electrolytes, particularly serum bicarbonate level, should be carried out in those patients with renal disease in order to avoid these complications.

ADVERSE REACTIONS

Sodium Citrate and Citric Acid Oral Solution USP is generally well tolerated, without any unpleasant side effects, when given in recommended doses to patients with normal renal function and urinary output. However, as with any alkalinizing agent, caution must be used in certain patients with abnormal renal mechanisms to avoid development of alkalosis, especially in the presence of hypocalcemia.

OVERDOSAGE

Overdosage with sodium salts may cause diarrhea, nausea and vomiting, hypernoia, and convulsions.

DOSAGE AND ADMINISTRATION

Sodium Citrate and Citric Acid Oral Solution USP should be taken diluted in water, followed by additional water, if desired. SHAKE WELL BEFORE USING.

For Systemic Alkalization

Usual Adult Dose

2 to 6 teaspoonfuls (10 to 30 mL), diluted in 1 to 3 ounces of water, after meals and at bedtime, or as directed by a physician.

Usual Pediatric Dose

1 to 3 teaspoonfuls (5 to 15 mL), diluted in 1 to 3 ounces of water, after meals and at bedtime, or as directed by a physician. For children under two years of age, use is based on consultation with a physician.

As a neutralizing buffer

3 teaspoonfuls (15 mL), diluted with 15 mL water, taken as a single dose, or as directed by a physician.

HOW SUPPLIED

NDC: 17856-0595-3 30 mL in a CUP

STORAGE:

Keep tightly closed. Store at controlled room temperature, 20°-25°C (68°-77°F). Protect from freezing.

Rx ONLY

Distributed by:

Atlantic Biologicals Corp.

Miami, FL 33179